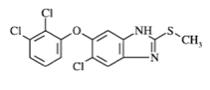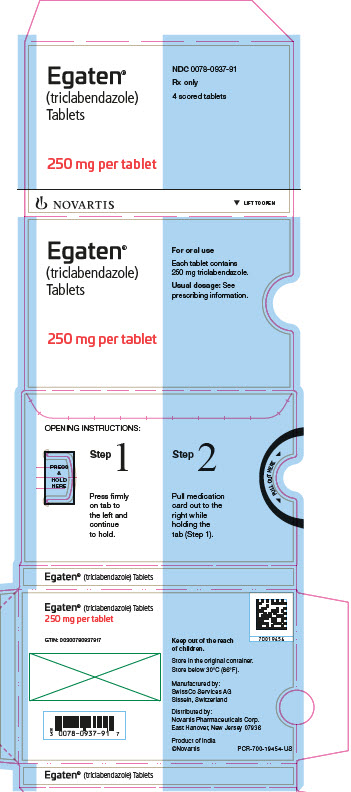 DRUG LABEL: EGATEN
NDC: 0078-0937 | Form: TABLET
Manufacturer: Novartis Pharmaceuticals Corporation
Category: prescription | Type: HUMAN PRESCRIPTION DRUG LABEL
Date: 20250305

ACTIVE INGREDIENTS: TRICLABENDAZOLE 250 mg/1 1
INACTIVE INGREDIENTS: LACTOSE MONOHYDRATE; STARCH, CORN; HYMETELLOSE (4150 MPA.S); MAGNESIUM STEARATE; SILICON DIOXIDE; FERRIC OXIDE RED

HIGHLIGHTS OF PRESCRIBING INFORMATION

These highlights do not include all the information needed to use EGATEN safely and effectively. See full prescribing information for EGATEN.
EGATEN® (triclabendazole) tablets, for oral use
Initial U.S. Approval: 2019

RECENT MAJOR CHANGES

Warnings and Precautions, QT Prolongation (5.1) | 2/2022

1 INDICATIONS AND USAGE

EGATEN® tablet is an anthelmintic indicated for the treatment of fascioliasis in patients 6 years of age and older.

2 DOSAGE AND ADMINISTRATION

- The recommended dose of EGATEN is 2 doses of 10 mg/kg given 12 hours apart in patients 6 years of age and older. (2)
- Take orally with food. (2)
- Swallow tablets whole or divide in half and take with water, or crush and administer with applesauce. (2)
- If the dosage cannot be adjusted exactly, round dose upwards. (2)

3 DOSAGE FORMS AND STRENGTHS

Tablets: 250 mg, functionally scored. (3)

4 CONTRAINDICATIONS

Patients with known hypersensitivity to triclabendazole, other benzimidazole derivatives or any of the excipients in EGATEN. (4)

5 WARNINGS AND PRECAUTIONS

QT Prolongation: Prolongs QTc interval. Monitor electrocardiogram (ECG) in patients with a history of QTc prolongation or with electrolyte imbalance like hypokalemia or who are taking medications which prolong the QTc interval, or on CYP1A2 inhibitors, or have hepatic impairment. (5.1)

6 ADVERSE REACTIONS

Most common adverse reactions (greater than 2%) with triclabendazole 20 mg/kg dose are abdominal pain, hyperhidrosis, nausea, decreased appetite, headache, urticaria, diarrhea, vomiting, musculoskeletal chest pain, and pruritus. (6.1)

To report SUSPECTED ADVERSE REACTIONS, contact Novartis Pharmaceuticals Corporation at 1-888-669-6682 or FDA at 1-800-FDA-1088 or www.fda.gov/medwatch.

7 DRUG INTERACTIONS

CYP2C19 Substrates: Re-check the plasma concentration of concomitantly administered CYP2C19 substrates after cessation of EGATEN therapy, if the plasma concentrations of the CYP2C19 substrates are elevated during administration of EGATEN. (7.1)

FULL PRESCRIBING INFORMATION

1 INDICATIONS AND USAGE

EGATEN® is indicated for the treatment of fascioliasis in patients 6 years of age and older.

2 DOSAGE AND ADMINISTRATION

The recommended dose of EGATEN is 2 doses of 10 mg/kg given 12 hours apart in patients 6 years of age and older. The 250 mg tablets are functionally scored and divisible into two equal halves of 125 mg. If the dosage cannot be adjusted exactly, round the dose upwards.

Take EGATEN orally with food. EGATEN tablets can be swallowed whole or divided in half and taken with water or crushed and administered with applesauce. The crushed tablet mixed with applesauce is stable for up to 4 hours.

3 DOSAGE FORMS AND STRENGTHS

EGATEN (triclabendazole) tablet: 250 mg pale red, speckled, capsule shaped, biconvex with “EG ⅁Ǝ” debossed on one side and functionally scored on both sides.

4 CONTRAINDICATIONS

EGATEN is contraindicated in patients with known hypersensitivity to triclabendazole and/or to other benzimidazole derivatives or to any of the excipients in EGATEN.

5 WARNINGS AND PRECAUTIONS

5.1 QT Prolongation

EGATEN prolongs the QTc interval [see Clinical Pharmacology (12.2)]. The magnitude of QTc prolongation can increase with increasing treatment duration of EGATEN. Administration of EGATEN concurrently with CYP1A2 inhibitors and use in patients with hepatic impairment may result in increased exposures of triclabendazole and/or its metabolites, and, therefore, may increase the risk for QT prolongation.

Monitor electrocardiogram (ECG) in patients with a history of prolongation of the QTc interval or a history of symptoms compatible with a long QT interval or with electrolyte imbalance like hypokalemia, or when EGATEN is used in patients who receive drugs that are known to prolong the QTc interval, or patients taking CYP1A2 inhibitors, or in patients with hepatic impairment. If signs of cardiac arrhythmia occur during treatment with EGATEN, stop the treatment and monitor ECG.

6 ADVERSE REACTIONS

6.1 Clinical Trials Experience

Because clinical trials are conducted under widely varying conditions, adverse reaction rates observed in the clinical trials of a drug cannot be directly compared to rates in clinical trials of another drug and may not reflect the rates observed in clinical practice.

The safety of triclabendazole was evaluated in 208 adult and pediatric patients 5 years of age and older who participated in 6 clinical trials for the treatment of fascioliasis and received 10 mg/kg or 20 mg/kg of triclabendazole; of these, 6 patients failed the 10 mg/kg dose and were retreated with 20 mg/kg. The 10 mg/kg dosing regimen is not approved [see Dosage and Administration (2)]. In these trials, 186 patients received a single dose of 10 mg/kg and 28 patients received a dose of 20 mg/kg as two divided doses. Pooled data for adverse reactions reported in more than 2% of the patients in these clinical trials for the 10 mg/kg and 20 mg/kg dosing regimens are presented in Table 1.

Table 1: Adverse Reactions Occurring in >2% of Patients Who Received a Total of 10 mg/kg or 20 mg/kg Triclabendazole for Fascioliasis Treatment (Pooled Across 6 Studies)
Adverse Reactions | Triclabendazole 10 mg/kg N = 186, n (%) | Triclabendazole 20 mg/kg in two divided doses^1 N = 28, n (%)
Abdominal pain^2 | 105 (56) | 26 (93)
Hyperhidrosis | 42 (23) | 7 (25)
Vertigo | 16 (9) | 0
Nausea | 15 (8) | 5 (18)
Urticaria | 12 (7) | 3 (11)
Vomiting | 11 (6) | 2 (7)
Headache | 11 (6) | 4 (14)
Dyspnea | 9 (5) | 0
Pruritus | 8 (4) | 1 (4)
Asthenia | 7 (4) | 0
Musculoskeletal chest pain | 7 (4) | 1 (4)
Cough | 7 (4) | 0
Decreased appetite | 6 (3) | 5 (18)
Chest pain | 6 (3) | 0
Pyrexia | 4 (2) | 0
Jaundice^3 | 4 (2) | 0
Chest discomfort | 4 (2) | 0
Diarrhea | 0 | 2 (7)
^1Divided doses were given 6-48 hours apart.
^2Abdominal pain upper and abdominal pain.
^3Jaundice and ocular icterus.

Adverse reactions reported in less than or equal to 2% of patients who received a total of 10 mg/kg of triclabendazole were constipation, biliary colic, arthralgia, back pain, spinal pain, and chromaturia. Some adverse reactions associated with triclabendazole treatment in fascioliasis, e.g., abdominal pain, biliary colic, and jaundice, could be secondary to the infection and may be more frequent and/or severe in patients with a heavy worm burden.

The safety profile of triclabendazole 20 mg/kg in divided doses in a non-hepatic parasitic infection (N = 104) was generally similar to the safety profile in fascioliasis, except for a lower incidence of post-treatment abdominal pain.

Liver Enzyme Elevations

In clinical studies, up to one third of patients had liver enzyme elevations at baseline, which generally improved post-treatment. Of those with normal liver enzyme values at baseline, 6.8%, 4.5%, 4.2% and 3% of patients had post-treatment elevations in bilirubin, aspartate aminotransferase (AST), alkaline phosphatase (ALP) and alanine aminotransferase (ALT), respectively. Transient increases in liver enzymes and total bilirubin in fascioliasis patients receiving triclabendazole are reported in the literature.

6.2 Postmarketing Experience

The following adverse reactions have been identified during post-marketing use of EGATEN. Because these reactions are reported voluntarily from a population of uncertain size, it is not always possible to reliably estimate their frequency or establish a causal relationship to drug exposure.

Resistance to triclabendazole has been reported [see Microbiology (12.4)].

7 DRUG INTERACTIONS

7.1 Effect of EGATEN on CYP2C19 Substrates

No specific clinical drug interaction studies have been conducted for triclabendazole. However, in vitro data suggest the potential for increased plasma concentrations of CYP2C19 substrates with concomitant use of triclabendazole [see Clinical Pharmacology (12.3)]. The potential elevation in concentrations of concomitantly used CYP2C19 substrates is expected to be transient based on the short elimination half-life and short treatment duration of triclabendazole.

For those CYP2C19 substrate drugs that require therapeutic monitoring of systemic drug exposures, if the plasma concentrations of the CYP2C19 substrates are elevated during administration of triclabendazole, re-check the plasma concentration of the CYP2C19 substrates after cessation of triclabendazole therapy.

8 USE IN SPECIFIC POPULATIONS

8.1 Pregnancy

Risk Summary

There are no available data on EGATEN use in pregnant women to inform a drug-associated risk of major birth defects, miscarriage or adverse maternal or fetal outcomes. Reproductive studies in animals (rat and rabbits) have not shown a risk of increased fetal abnormalities with exposure to triclabendazole during organogenesis at doses approximately 0.3 to 1.6 times the maximum recommended human dose (MRHD) of 20 mg/kg based on body surface area comparison (see Data).

The estimated background risk of major birth defects and miscarriage for the indicated population are unknown. All pregnancies have a background risk of birth defect, loss, or other adverse outcomes. In the U.S. general population, the estimated background risk of major birth defects and miscarriage in clinically recognized pregnancies is 2%-4% and 15%-20%, respectively.

Data

Animal Data

Embryo-fetal developmental toxicity studies revealed no malformations in rats and rabbits at doses up to 200 mg/kg/day and 20 mg/kg/day, respectively (approximately 1.6 times and 0.3 times the MRHD based on body surface area comparison, respectively). The animals were treated orally during organogenesis, starting on Day 6 of the pregnancy until Day 15 in rats and Day 18 in rabbits. Maternal toxicity was noted at doses greater than or equal to 100 mg/kg/day in rats and 10 mg/kg/day in rabbits, which was associated with lower fetus weights and delayed ossification. These findings were considered indicative of delayed physiological growth that was secondary to maternal toxicity. No increase in malformation or other abnormalities was observed at any dose level in either species.

8.2 Lactation

Risk Summary

There are no data on the presence of triclabendazole in human milk, the effects on the breastfed infant, or the effects on milk production. Published animal data indicate that triclabendazole is detected in goat milk when administered as a single dose to one lactating animal. When a drug is present in animal milk, it is likely that the drug will be present in human milk. The developmental and health benefits of breastfeeding should be considered along with the mother’s clinical need for EGATEN and any potential adverse effects on the breastfed infant from EGATEN or from the underlying maternal condition.

8.4 Pediatric Use

Safety and effectiveness of EGATEN has been established in pediatric patients aged 6 years and older.

Safety and effectiveness of EGATEN in pediatric patients below the age of 6 years have not been established.

8.5 Geriatric Use

Clinical studies of EGATEN did not include sufficient numbers of patients aged 65 and over to determine whether the elderly respond differently from younger patients. In general, dose selection for an elderly patient should be cautious, reflecting the greater frequency of decreased hepatic, renal, or cardiac function, and of concomitant disease or other drug therapy.

8.6 Renal Impairment

EGATEN has not been studied in patients with renal impairment.

8.7 Hepatic Impairment

EGATEN has not been studied in patients with hepatic impairment.

10 OVERDOSAGE

The reported symptom of overdosage following ingestion of approximately 54 mg/kg of EGATEN (approximately 2.7 times the recommended dose) was nausea. The patient recovered following osmotic diuresis. In the event of overdose, monitor ECG and institute symptomatic treatment.

11 DESCRIPTION

EGATEN (triclabendazole) tablet is an orally administered anthelmintic for immediate release. Triclabendazole is designated chemically as benzimidazole derivative, 6-chloro-5-(2, 3-dichlorophenoxy)-2-(methylthio)-1H-benzimidazole (triclabendazole). The molecular formula for triclabendazole is C14H9Cl3N2OS and the molecular weight is 359.65 g/mol. The chemical structure of triclabendazole is shown below:

Triclabendazole is a white or almost white, crystalline powder.

EGATEN tablets are pale red, speckled, capsule shaped, biconvex tablets, with “EG ⅁Ǝ” debossed on one side and functionally scored on both sides. Each tablet contains 250 mg of triclabendazole.

Inactive Ingredients: colloidal silicon dioxide, iron oxide red, lactose monohydrate, maize starch, magnesium stearate, methylhydroxyethylcellulose.

12 CLINICAL PHARMACOLOGY

12.1 Mechanism of Action

Triclabendazole is an anthelmintic against Fasciola species [see Microbiology (12.4)].

12.2 Pharmacodynamics

Triclabendazole exposure-response relationships and the time course of pharmacodynamics response are unknown.

Cardiac Electrophysiology

Dose-dependent prolongation in the QTc interval was observed with EGATEN in a randomized, partially blinded, placebo- and moxifloxacin-controlled, 4-period cross-over study in healthy subjects. The largest placebo-corrected mean increase in QTc was 9.2 msec (upper limit of confidence interval (UCI): 12.2 msec) following oral administration of 10 mg/kg EGATEN twice daily (at the recommended dose), and the largest placebo-corrected mean increase in QTc was 21.7 msec (UCI: 24.7 msec) following oral administration of 10 mg/kg EGATEN twice daily for 3 days (3 times the approved recommended dosing duration) [see Warnings and Precautions (5.1)].

12.3 Pharmacokinetics

After oral administration of a single dose of 10 mg/kg triclabendazole with a 560-kcal meal to patients with fascioliasis, mean peak plasma concentrations (Cmax) for triclabendazole, the sulfoxide and sulfone metabolites were 1.16, 38.6, and 2.29 μmol/L, respectively. The area under the curve (AUC) for triclabendazole, the sulfoxide and sulfone metabolites were 5.72, 386, and 30.5 μmol∙h/L, respectively.

Absorption

Following oral administration of a single dose of triclabendazole at 10 mg/kg with a 560-kcal meal to patients with fascioliasis, the median Tmax for the parent compound and the sulfoxide metabolite was 3 to 4 hours.

Effect of Food

Cmax and AUC of triclabendazole and sulfoxide metabolite increased approximately 3-fold and 2-fold, respectively, when triclabendazole was administered as a single dose at 10 mg/kg with a meal containing a total of approximately 560 kcal (consisting of 2 cups of sweetened white coffee, a roll with cheese, and a roll with butter and jam). In addition, the sulfoxide metabolite Tmax increased from 2 hours in the fasted state to 4 hours in the fed state.

Distribution

The apparent volume of distribution (Vd) of the sulfoxide metabolite in fed patients is approximately 1 L/kg.

Protein-binding of triclabendazole, sulfoxide metabolite and sulfone metabolite in human plasma was 96.7%, 98.4% and 98.8%, respectively.

Elimination

The plasma elimination half-life (t1/2) of triclabendazole, the sulfoxide and sulfone metabolites in humans is approximately 8, 14, and 11 hours, respectively.

Metabolism

Based on in vitro studies, triclabendazole is primarily metabolized by CYP1A2 (approximately 64%) into its active sulfoxide metabolite and to a lesser extent by CYP2C9, CYP2C19, CYP2D6, CYP3A, and FMO. This sulfoxide metabolite is further metabolized primarily by CYP2C9 to the active sulfone metabolite and to a lesser extent by CYP1A1, CYP1A2, CYP1B1, CYP2C19, CYP2D6 and CYP3A4, in vitro.

Excretion

No excretion data is available in humans. However, in animals, the drug is largely excreted via the biliary tract in the feces (90%), together with the sulfoxide and sulfone metabolite. Less than 10% of an oral dose is excreted in the urine.

Specific Populations

The pharmacokinetics of EGATEN were not studied in patients with renal or hepatic impairment.

Pediatric Patients

No dedicated pediatric pharmacokinetic studies were conducted. However, in one pharmacokinetic study of 20 patients, 7 children (ages 9 to 15 years) were dosed with triclabendazole 10 mg/kg single dose. AUC values of triclabendazole sulfoxide were 20% lower in these pediatric patients in the fed state than in the 13 patients above 15 years of age, but the difference was not statistically significant.

Drug Interaction Studies:

Clinical drug interaction studies have not been conducted for triclabendazole.

In Vitro Studies

Triclabendazole and its sulfoxide and sulfone metabolites have the potential to inhibit CYP1A2, CYP2A6, CYP2B6, CYP2C8, CYP2C9, CYP2C19, CYP2D6, and CYP3A at clinically relevant plasma concentrations, with the highest potential of inhibition on CYP2C19. No in vitro studies were conducted to assess the ability of triclabendazole and its metabolites to induce CYP enzymes. No in vitro studies were conducted to assess the ability of triclabendazole and its metabolites to induce or inhibit transporters.

12.4 Microbiology

Mechanism of Action

The mechanism by which triclabendazole exhibits its effect against Fasciola species is not fully elucidated. Studies in vitro and/or in infected animals suggest that triclabendazole and its active metabolites (sulfoxide and sulfone) are absorbed by the tegument of the immature and mature worms, leading to a decrease of the resting membrane potential, inhibition of tubulin function as well as protein and enzyme synthesis. These metabolic disturbances are associated with inhibition of motility, disruption of the surface as well as ultrastructure that includes inhibition of spermatogenesis and vitelline cells.

Antimicrobial Activity

Triclabendazole and its metabolites are active against the immature and mature worms of Fasciola hepatica and Fasciola gigantica [see Clinical Studies (14)].

Resistance

Studies in vitro and in vivo as well as case reports suggest a potential for development of resistance to triclabendazole.

The mechanism of resistance may be multifactorial that include changes in drug uptake/efflux mechanisms, the target molecules, and altered drug metabolism. The clinical significance of triclabendazole resistance in humans is not established.

13 NONCLINICAL TOXICOLOGY

13.1 Carcinogenesis, Mutagenesis, Impairment of Fertility

Mutagenesis

No genotoxic potential was noted for triclabendazole tested in a battery of 6 genotoxicity in vitro and in vivo assays which include a bacterial reverse mutation assay, chromosome aberration assays, and a micronucleus assay.

Impairment of Fertility

No drug-related effects on reproductive performance, mating ratios or fertility indices have been noted in a 2-generation reproductive and developmental toxicity study in rats. The animals were treated with up to 75 ppm triclabendazole via diet, amounting to a mean daily intake of 7.3 mg/kg/day (approximately 0.1 times the MRHD based on body surface area comparison) for a period of 110 days, which included a 12-day mating period beginning on Day 62 of dosing and continuing until the offspring were weaned.

13.2 Animal Toxicology and/or Pharmacology

Dietary administration of triclabendazole at a dose of 39 mg/kg/day (1.1-times the MRHD based on body surface area comparison) was associated with a transient increase in the QT and QTc intervals on Weeks 5 and 9 in some dogs in a 13-week study resulting in QT (QTc) intervals of 212-227 (318-338) msec in the 39 mg/kg dose group (adjusted) compared to 190-193 (280-297) msec in controls. At Week 13, no statistically significant differences were noted between the treatment and control groups.

Additionally, when dogs were administered triclabendazole at a single dose of 40 or 100 mg/kg (1.1 or 2.7 times the MRHD based on body surface area comparison), increase in QTc intervals was observed resulting in QTc intervals of 217-247 msec compared to a normal (historical control) of 193-231 msec.

In the 13-week study in beagle dogs, slight anemia accompanied by minimal increases in reticulocyte and nucleated red cell counts were observed at 39 mg/kg/day (1.1 times the MRHD based on body surface area comparison) predominantly at Week 9 of dosing.

14 CLINICAL STUDIES

An open label, randomized trial, conducted in Vietnam compared the efficacy of triclabendazole (two 10 mg/kg doses given 12 hours apart with food) to oral artesunate (4 mg/kg, given once daily for 10 days). One hundred patients (age range: 9-74 years) with acute symptomatic fascioliasis were randomized, 50 in each treatment group. At 3 months after treatment, 92% and 76% (difference 16%; 95% CI [1.7, 30.8], p = 0.035) of patients in the triclabendazole and artesunate arms, respectively, reported no clinical symptoms.

The clinical development program of triclabendazole for the treatment of fascioliasis included 6 non-randomized, open label studies performed in Cuba, Bolivia, Peru, Chile, and Iran in a total of 245 adult and pediatric patients with stool-confirmed fascioliasis. All studies were similar in design. The studied triclabendazole doses ranged from 5 mg/kg to 20 mg/kg administered on Days 1-3. Cure was defined as absence of Fasciola eggs in the stool based on the Kato-Katz method at Day 60 in patients who were positive at baseline. Across these studies, there was a finding of a dose response. Specifically, the Day 60 cure rate was highest (95.5%; 95% CI [77%, 100%]) for the 20 mg/kg dose, which was given in 2 divided doses, followed by cure rates of 88% (95% CI [64%, 99%]), 80% (95% CI [73%, 86%]), and 50% (95% CI [27%, 73%]) in the 15 mg/kg, 10 mg/kg, and 5 mg/kg dose groups, respectively. The 5 mg/kg, 10 mg/kg, and 15 mg/kg dosing regimens are not approved [see Dosage and Administration (2)]. These rates were significantly higher than that estimated from patients receiving an inadequate, non-triclabendazole treatment in a separate study (22%; 95% CI [9.8, 38.2]).

16 HOW SUPPLIED/STORAGE AND HANDLING

How Supplied

EGATEN (triclabendazole) tablets are supplied as pale red, speckled, capsule shaped, biconvex tablets with “EG ⅁Ǝ” debossed on one side and functionally scored on both sides. Each tablet contains 250 mg of triclabendazole. EGATEN (triclabendazole) tablets are available as:

Blister packs of 4 tablets (NDC 0078-0937-91).

Storage

Store in the original container. Store below 30°C (86°F).

17 PATIENT COUNSELING INFORMATION

Important Administration Instructions

Advise patients that EGATEN should be taken orally with food. The tablets can be swallowed whole or divided in half and taken with water or crushed and administered with applesauce. The crushed tablet mixed with applesauce is stable for up to 4 hours [see Dosage and Administration (2)].

QT Prolongation

Advise patients with a history of prolongation of the QTc interval or a history of symptoms compatible with a long QT interval or with electrolyte imbalance like hypokalemia or when EGATEN is used in patients who receive drugs that are known to prolong the QTc interval or on CYP1A2 inhibitors or have hepatic impairment that their ECGs will need to be monitored [see Warnings and Precautions (5.1)].

Distributed by:

Novartis Pharmaceuticals Corporation

East Hanover, New Jersey 07936

For more information on EGATEN, call 1-888-669-6682.

© Novartis

T2022-10

PRINCIPAL DISPLAY PANEL

Egaten®

(triclabendazole)
Tablets

250 mg per tablet

NDC 0078-0937-91

Rx only

4 scored tablets

Novartis